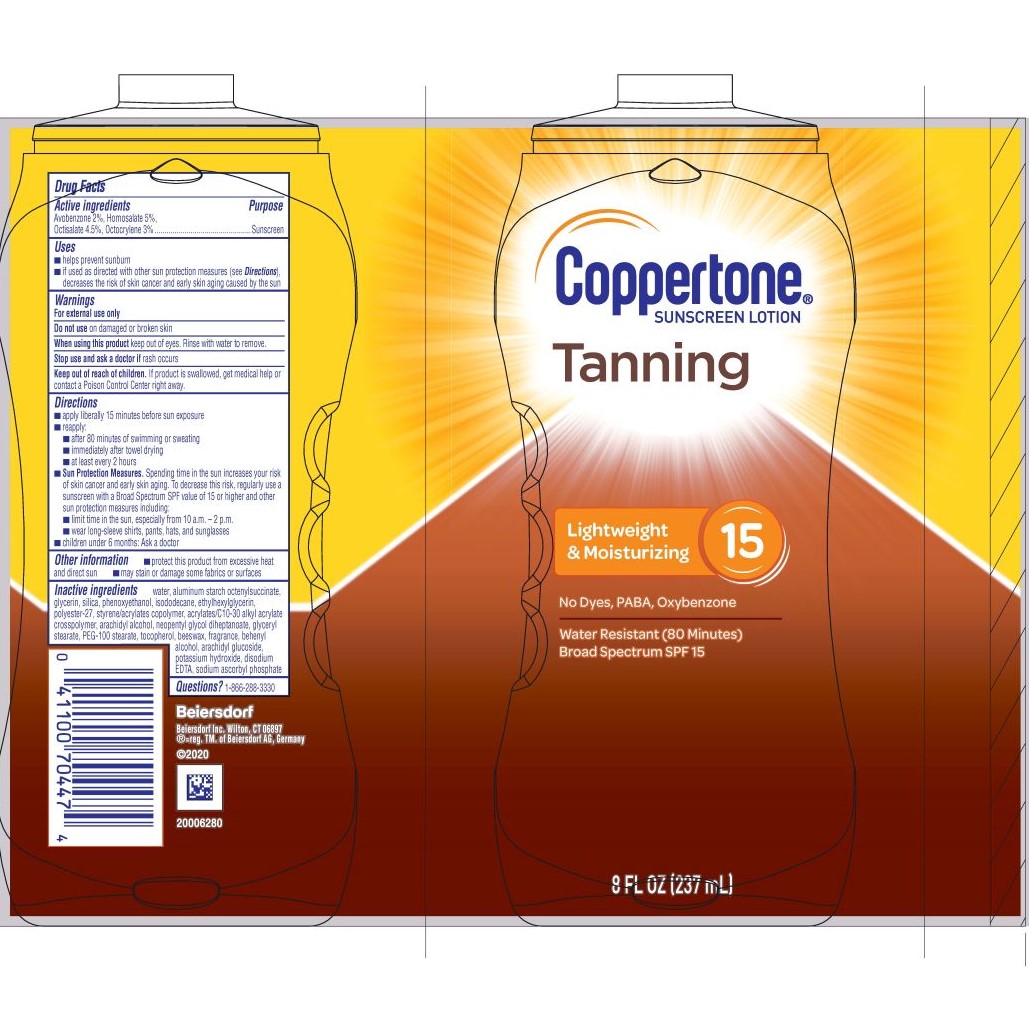 DRUG LABEL: Coppertone Tanning Sunscreen SPF 15
NDC: 66800-4087 | Form: LOTION
Manufacturer: Beiersdorf Inc
Category: otc | Type: HUMAN OTC DRUG LABEL
Date: 20251231

ACTIVE INGREDIENTS: AVOBENZONE 2 g/100 g; OCTISALATE 4.5 g/100 g; HOMOSALATE 5 g/100 g; OCTOCRYLENE 3 g/100 g
INACTIVE INGREDIENTS: NEOPENTYL GLYCOL DIHEPTANOATE; ARACHIDYL ALCOHOL; SYNTHETIC BEESWAX; PEG-100 STEARATE; ARACHIDYL GLUCOSIDE; DISODIUM EDTA-COPPER; SODIUM ASCORBYL PHOSPHATE; POLYESTER-7; FRAGRANCE FLORAL ORC0902236; POTASSIUM HYDROXIDE; GLYCERYL STEARATE SE; WATER; GLYCERIN; PHENOXYETHANOL; SILICON DIOXIDE; ISODODECANE; ETHYLHEXYLGLYCERIN; STYRENE/ACRYLAMIDE COPOLYMER (MW 500000); ALUMINUM STARCH OCTENYLSUCCINATE; DOCOSANOL; ACRYLATES CROSSPOLYMER-6

Tanning Lotion SPF 15

Active ingredients

Avobenzone 2%, Homosalate 5%, Octisalate 4.5%, Octocrylene 3%

Purpose

Sunscreen

Use

■ helps prevent sunburn

Warnings

For external use only

Do not useon damaged or broken skin

WHEN USING

When using this productkeep out of eyes. Rinse with water to remove.

Stop use and ask a doctor ifrash occurs

Keep out of reach of children.If product is swallowed, get medical help or contact a Poison Control Center right away.

Directions

■ apply liberally 15 minutes before sun exposure

■ reapply:

■ after 80 minutes of swimming or sweating

■ immediately after towel drying

■ at least every 2 hours

■ children under 6 months: Ask a doctor

Other information

■ protect this product from excessive heat and direct sun

■ may stain or damage some fabrics or surfaces

Inactive ingredients

water, aluminum starch octenylsuccinate, glycerin, silica, phenoxyethanol, isododecane, ethylhexylglycerin, polyester-27, styrene/acrylates copolymer, acrylates/C10-30 alkyl acrylate crosspolymer, arachidyl alcohol, neopentyl glycol diheptanoate, glyceryl stearate, PEG-100 stearate, beeswax, fragrance, behenyl alcohol, arachidyl glucoside, potassium hydroxide, disodium EDTA, sodium ascorbyl phosphate

Questions?

1-866-288-3330

PACKAGE LABEL

Coppertone®Sunscreen Lotion

Tanning

Lightweight & Moisturizing 15

No Dyes, PABA, Oxybenzone

Water Resistant (80 Minutes)

8 FL OZ (237 mL)